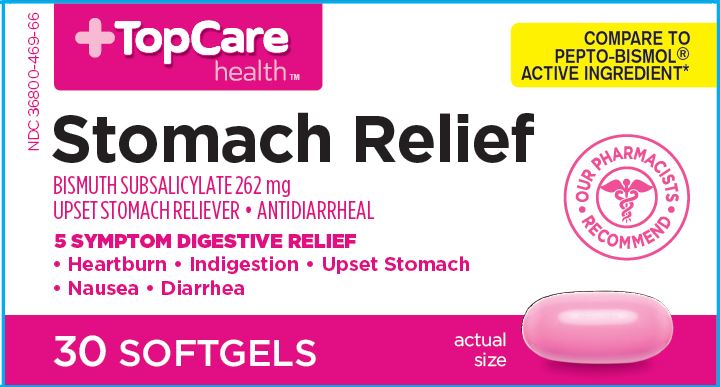 DRUG LABEL: Stomach Relief
NDC: 36800-134 | Form: CAPSULE, LIQUID FILLED
Manufacturer: TOP CARE (Topco Associates LLC)
Category: otc | Type: HUMAN OTC DRUG LABEL
Date: 20241220

ACTIVE INGREDIENTS: BISMUTH SUBSALICYLATE 262 mg/1 1
INACTIVE INGREDIENTS: SILICON DIOXIDE; YELLOW WAX; D&C RED NO. 33; FD&C YELLOW NO. 6; GELATIN; GLYCERIN; PARAFFIN; WATER; LECITHIN, SOYBEAN; CARBOXYMETHYLCELLULOSE; SORBITOL; TITANIUM DIOXIDE

TopCare health Stomach Relief - Bismuth Subsalicylate 262mg

Drug Facts

ACTIVE INGREDIENT

Active ingredient Purpose

(in each softgel)

Bismuth subsalicylate 262 mg...............Upset stomach reliever and anti-diarrheal

Uses

relieves

- travelers' diarrhea
- diarrhea
- upset stomach due to overindulgence in food and drink, including:
  - heartburn
  - indigestion
  - nausea
  - gas
  - belching
  - fullness

Warnings

Reye's syndrome

Children and teenagers who have or are recovering from chicken pox or flu-like symptoms should not use this product. When using this product, if changes in behavior with nausea and vomiting occur, consult a doctor because these symptoms could be an early sign of Reye's syndrome, a rare but serious illness.

Allergy alert

Contains salicylate. Do not take if you are

- allergic to salicylates (including aspirin)
- taking other salicylate products

Do not use ifyou have

- an ulcer
- a bleeding problem
- bloody or black stool

Ask a doctor before use if you have

- fever
- mucus in the stool

Ask a doctor or pharmacist before use if you are taking any drug for

- anticoagulation (thinning the blood)
- diabetes
- gout
- arthritis

When using this product a temporary, but harmless, darkening of the stool and/or tongue may occur

Stop use and ask a doctor if

- symptoms get worse or last more than 2 days
- ringing in the ears or loss of hearing occurs
- diarrhea lasts more than 2 days

PREGNANCY OR BREAST FEEDING

If pregnant or breast feeding, ask a health professional before use.

Keep out of reach of children. In case of overdose, get medical help or contact a Poison Control Center right away.

Directions

- swallow with water, do not chew
- adults and children 12 years and over:
- 2 softgels (1 dose) every 1/2 hour or 4 softgels (2
  doses) every hour as needed for diarrhea
- 2 softgels (1 dose) every 1/2 hour as needed for overindulgence (upset stomach, heartburn, indigestion, nausea)
- do not exceed 8 doses (16 softgels) in 24 hours
- use until diarrhea stops but not more than 2 days
- children under 12 years: ask a doctor
- drink plenty of clear fluids to help prevent dehydration caused by diarrhea

Other information

each softgel contains:

• salicylate 99 mg • very low sodium

• store between 15-30°C (59-86°F)

Inactive ingredients

aerosil, beeswax, FD&C Red#33. FD&C Yellow#6, gelatin, glycerin, light liquid paraffin, purified water, soya lecithin, sodium carboxy methyl
cellulose, sorbitol solution, titanium dioxide

Questions or comments?

1-888-333-9792

PRINCIPAL DISPLAY PANEL

TopCare health ™

Stomach Relief

BISMUTH SUBSALICYLATE
UPSET STOMACH RELIEVER / ANTIDIARRHEAL

5 SYMPTOM Digestive Relief

heartburn
indigestion
nausea
upset stomach
diarrhea
30 Softgels